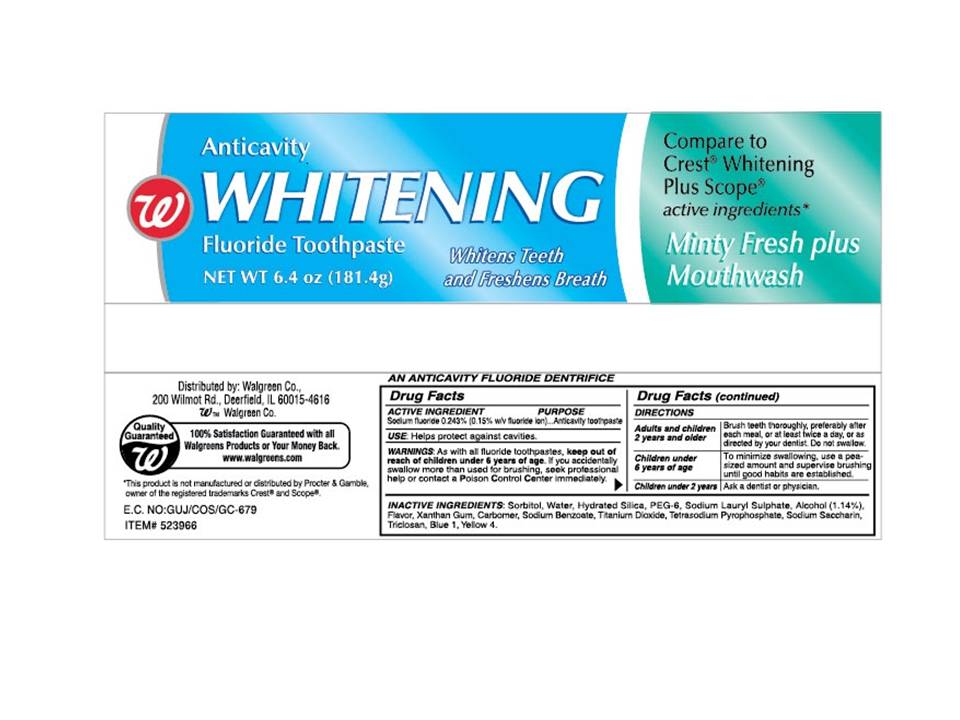 DRUG LABEL: Walgreen Anticavity Whitening 
NDC: 0363-0634 | Form: PASTE, DENTIFRICE
Manufacturer: Walgreen
Category: otc | Type: HUMAN OTC DRUG LABEL
Date: 20110219

ACTIVE INGREDIENTS: Sodium Fluoride 2.43 mg/1 g
INACTIVE INGREDIENTS: Sorbitol; Water; Silicon Dioxide; POLYETHYLENE GLYCOL 300; Sodium Lauryl Sulfate; Alcohol .0114 g/1 g; XANTHAN GUM; CARBOMER 934; SODIUM BENZOATE; TITANIUM DIOXIDE; SODIUM PYROPHOSPHATE; SACCHARIN SODIUM; TRICLOSAN

Anticavity Whitening Toothpaste Minty Fresh plus Mouthwash

USE

Helps protect against cavities.

WARNINGS

As with all fluoride toothpaste, keep out of reach of children under 6 years of age. If you accidentally swallow more than used for brushing, seek professional help or contact the Poison Control Center immediately.

Directions

Adults and children Brush teeth throughly, preferably after
2 years and older each meal, or at least twice a day, or as
directed by your dentist. Do not swallow.

Children under To minimize swallowing, use a pea-
6 years of age sized amount and supervise brushing
until good habits are established.

Children under 2 years Ask a dentist or physician.

Inactive Ingredients:

Sorbitol, Water, Hydrated Silica, PEG-6, Sodium Lauryl Sulphate, Alcohol (1.14%), Flavor, Xanthan Gum, Carbomer, Sodium Benzoate, Titanium Dioxide, Tetrasodium Pyrophoshate, Sodium Saccharin, Triclosan, Blue 1, Yellow 4.

Active Ingredient

Sodium Fluoride 0.243% (0.15% w/v fluoride ion)...Anticavity toothpaste